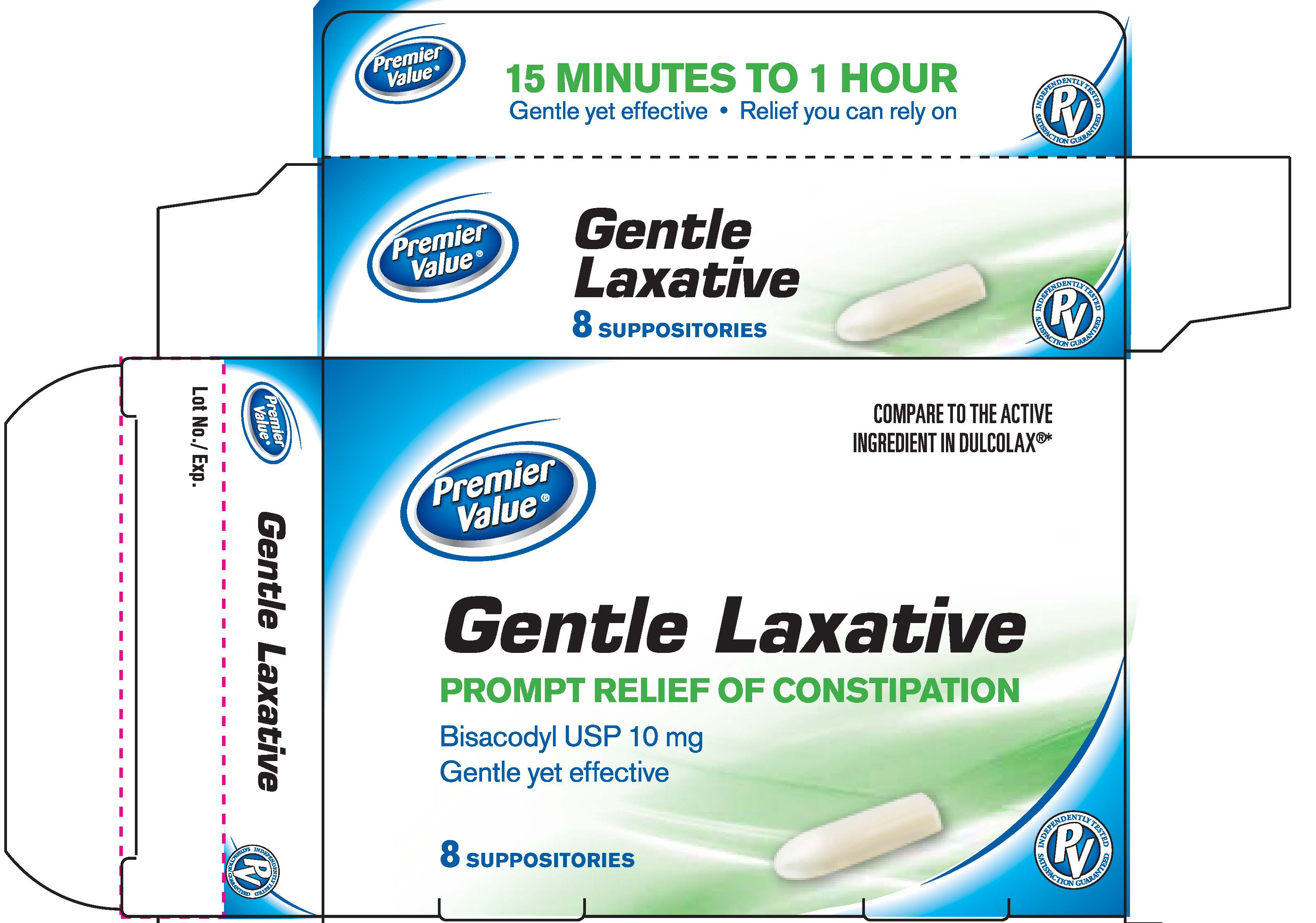 DRUG LABEL: Bisacodyl							
NDC: 68016-084 | Form: SUPPOSITORY
Manufacturer: Pharmacy Value Alliance LLC
Category: otc | Type: HUMAN OTC DRUG LABEL
Date: 20251024

ACTIVE INGREDIENTS: BISACODYL 10 mg/1 1
INACTIVE INGREDIENTS: HYDROGENATED PALM KERNEL OIL

Premier Value Bisacodyl Supp

Active ingredient (in each suppository)

Bisacodyl USP 10mg

Purpose

Stimulant Laxative

Use

- for temporary relief of occasional constipation and irregularity
- this product generally produces bowel movement in 15 minutes to 1 hour

Warnings

For rectal use only

Ask a Doctor before using any laxative if you have

- stomach pain, nausea or vomiting
- a sudden change in bowel habits that lasts more than 2 weeks

When using this product

it may cause stomach discomfort, faintness, rectal burning and mild cramps

Stop use and ask a doctor if

- you have rectal bleeding or no bowel movement after using laxative products. These could be signs of a very serious condition.
- you need to use a laxative for more than 1 week

If pregnant or breast feeding,

ask a health professional before use.

Keep out of reach of children.

If swallowed, get medical help or contact a Poison Control Center right away.

Directions

adults and children 12 years of age and over - 1 suppository in a single daily dose. Peel open plastic. Insert suppository well into rectum, pointed end first. Retain about 15 to 20 minutes.

children 6 to under 12 years of age - 1/2 suppository in a sinle daily dose

children under 6 years of age - ask a doctor

Other information

- do not store above 30ºC (86ºF)

Inactive ingredients

hydrogenated vegetable oil

Premier Value Bisacodyl Suppositories

PVBisacodyl8.jpg

The product package shown above represents a sample of that currently in use. Additional packaging may also be available.

Bisacodyl Suppositories 8ct

Distributed by

Pharmacy Value Alliance, LLC

407 East Lancaster Avenue

Wayne, PA 19087